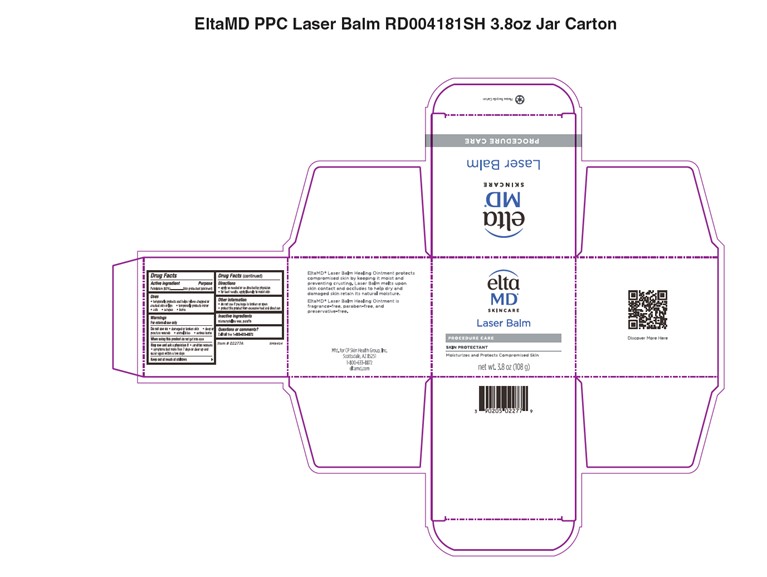 DRUG LABEL: EltaMD Laser Balm
NDC: 72043-2277 | Form: OINTMENT
Manufacturer: CP Skin Health Group, Inc
Category: otc | Type: HUMAN OTC DRUG LABEL
Date: 20231109

ACTIVE INGREDIENTS: PETROLATUM 600 g/1000 g
INACTIVE INGREDIENTS: PARAFFIN; MICROCRYSTALLINE WAX

EltaMD Laser Balm

Warnings

For external use only. Do not use on damaged or broken skin. When using this product do not get into eyes. Stop use and ask a physician if condition worsens, symptoms last more than 7 days or clear up and occur again within a few days.

Active Ingredient

Petrolatum 60% Skin Protectant

Uses

Temporarily protects and helps relieve chapped or cracked skin or lips.

Temporarily protects minor cuts, scrapes and burns.

Directions

Apply as needed or as directd by physician. For best results, apply liberally to moist skin.

Directions

Apply as needed or as directd by physician. For best results, apply liberally to moist skin.

Keep out of reach of children

Inactive Ingredients

mircocrystalline wax, paraffin